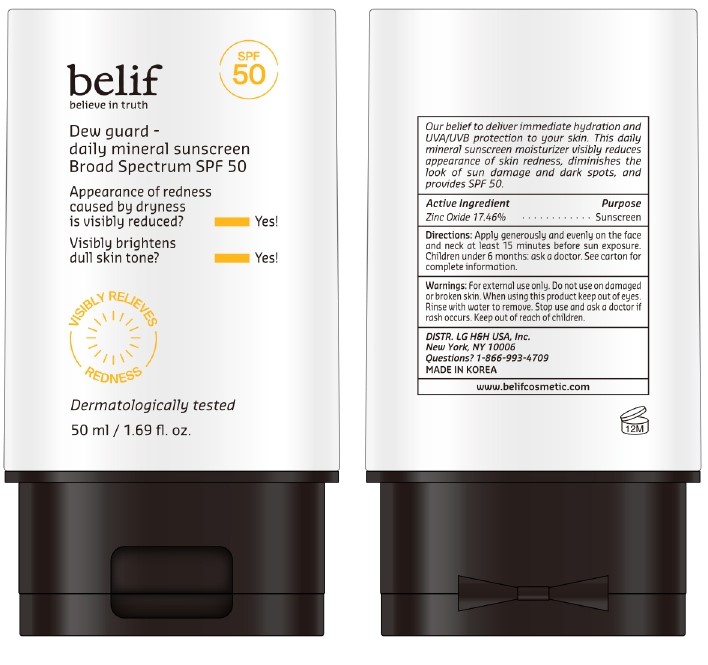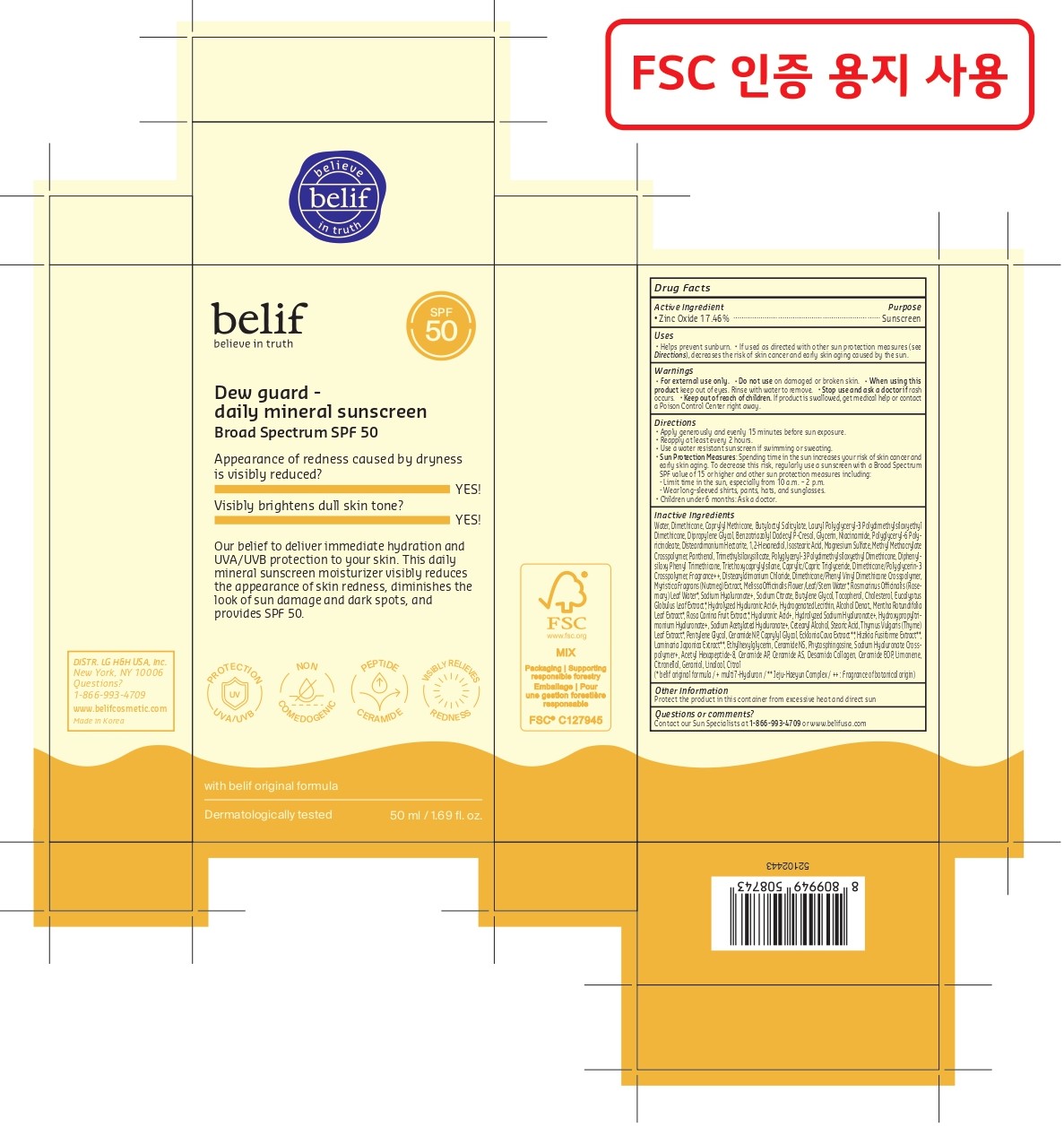 DRUG LABEL: belif Dew guard - daily mineral sunscreen Broad Spectrum SPF 50
NDC: 53208-740 | Form: CREAM
Manufacturer: LG H&H CO., LTD.
Category: otc | Type: HUMAN OTC DRUG LABEL
Date: 20250313

ACTIVE INGREDIENTS: ZINC OXIDE 17.46 g/100 g
INACTIVE INGREDIENTS: CERAMIDE NS; PHYTOSPHINGOSINE; ACETYL HEXAPEPTIDE-8; PENTYLENE GLYCOL; NIACINAMIDE; HYALURONIC ACID; CETEARYL ALCOHOL; SODIUM CITRATE; BUTYLENE GLYCOL; THYMUS VULGARIS (THYME) LEAF; DIMETHICONE/PHENYL VINYL DIMETHICONE CROSSPOLYMER; CITRAL; DISTEARDIMONIUM HECTORITE; 1,2-HEXANEDIOL; ISOSTEARIC ACID; NUTMEG; ROSMARINUS OFFICINALIS (ROSEMARY) LEAF OIL; CHOLESTEROL; EUCALYPTUS GLOBULUS LEAF; ECKLONIA CAVA; LIMONENE, (+)-; BENZOTRIAZOLYL DODECYL P-CRESOL; DIPROPYLENE GLYCOL; CAPRYLYL GLYCOL; ETHYLHEXYLGLYCERIN; CAPRYLYL METHICONE; BUTYLOCTYL SALICYLATE; DEHYDRATED ALCOHOL; DIMETHICONE; POLYGLYCERYL-6 POLYRICINOLEATE; MAGNESIUM SULFATE; POLYGLYCERYL-3 POLYDIMETHYLSILOXYETHYL DIMETHICONE (4000 MPA.S); TRIETHOXYCAPRYLYLSILANE; CAPRYLIC/CAPRIC TRIGLYCERIDE; DIMETHICONE/POLYGLYCERIN-3 CROSSPOLYMER; TOCOPHEROL; ROSA CANINA FRUIT; CERAMIDE NP; CERAMIDE AP; DISTEARYLDIMONIUM CHLORIDE; SODIUM ACETYLATED HYALURONATE; SODIUM HYALURONATE; PANTHENOL; LAMINARIA JAPONICA; CITRONELLOL; GERANIOL; LINALOOL; WATER; DIPHENYLSILOXY PHENYL TRIMETHICONE; MELISSA OFFICINALIS FLOWERING TOP; MENTHA X ROTUNDIFOLIA LEAF; GLYCERIN; LAURYL POLYGLYCERYL-3 POLYDIMETHYLSILOXYETHYL DIMETHICONE (4000 MPA.S); STEARIC ACID; SARGASSUM FUSIFORME

Active Ingredient

Zinc Oxide 17.46%

Purpose

Sunscreen

Uses

- Helps prevent sunburn.
- If used as directed with other sun protection measures (see Directions), decreases the risk of skin cancer and early skin aging caused by the sun.

WARNINGS

For external use only.

Do not use on damaged or broken skin.

When using this product keep out of eyes. Rinse with water to remove.

Stop use and ask a doctor if rash occurs.

Keep out of reach of children.

DOSAGE AND ADMINISTRATION

If product is swallowed, get medical help or contact a Poison Control Center right away.

Directions

- Apply generously and evenly 15 minutes before sun exposure.
- Reapply at least every 2 hours.
- Use a water resistant sunscreen if swimming or sweating.
- Sun Protection Measures: Spending time in the sun increases your risk of skin cancer and early skin aging. To decrease this risk, regularly use a sunscreen with a Broad Spectrum SPF value of 15 or higher and other sun protection measures including:
  - Limit time in the sun, especially from 10 a.m. – 2 p.m.
  - Wear long-sleeved shirts, pants, hats, and sunglasses.
- Children under 6 months: Ask a doctor.

Inactive Ingredients

Water, Dimethicone, Caprylyl Methicone, Butyloctyl Salicylate, Lauryl Polyglyceryl-3 Polydimethylsiloxyethyl Dimethicone, Dipropylene Glycol, Benzotriazolyl Dodecyl P-Cresol, Glycerin, Niacinamide, Polyglyceryl-6 Polyricinoleate, Disteardimonium Hectorite, 1,2-Hexanediol, Isostearic Acid, Magnesium Sulfate, Methyl Methacrylate Crosspolymer, Panthenol, Trimethylsiloxysilicate, Polyglyceryl-3 Polydimethylsiloxyethyl Dimethicone, Diphenylsiloxy Phenyl Trimethicone, Triethoxycaprylylsilane, Caprylic/Capric Triglyceride, Dimethicone/Polyglycerin-3 Crosspolymer, Fragrance++, Distearyldimonium Chloride, Dimethicone/Phenyl Vinyl Dimethicone Crosspolymer, Myristica Fragrans (Nutmeg) Extract, Melissa Ocinalis Flower/Leaf/Stem Water*, Rosmarinus Ocinalis (Rosemary) Leaf Water*, Sodium Hyaluronate+, Sodium Citrate, Butylene Glycol, Tocopherol, Cholesterol, Eucalyptus Globulus Leaf Extract*, Hydrolyzed Hyaluronic Acid+, Hydrogenated Lecithin, Alcohol Denat., Mentha Rotundifolia Leaf Extract*, Rosa Canina Fruit Extract*, Hyaluronic Acid+, Hydrolyzed Sodium Hyaluronate+, Hydroxypropyltrimonium Hyaluronate+, Sodium Acetylated Hyaluronate+, Cetearyl Alcohol, Stearic Acid, Thymus Vulgaris (Thyme) Leaf Extract*, Pentylene Glycol, Ceramide NP, Caprylyl Glycol, Ecklonia Cava Extract**, Hizikia Fusiforme Extract**, Laminaria Japonica Extract**, Ethylhexylglycerin, Ceramide NS, Phytosphingosine, Sodium Hyaluronate Crosspolymer+, Acetyl Hexapeptide-8, Ceramide AP, Ceramide AS, Desamido Collagen, Ceramide EOP, Limonene, Citronellol, Geraniol, Linalool, Citral.

(* belif original formula / + multi7-Hyaluron / ** Jeju-Haeyun Complex / ++ : Fragrance of botanical origin)

Other Information

Protect the product in this container from excessive heat and direct sun

Questions or comments?

Contact our Sun Specialists at 1-866-993-4709 or www.belifusa.com